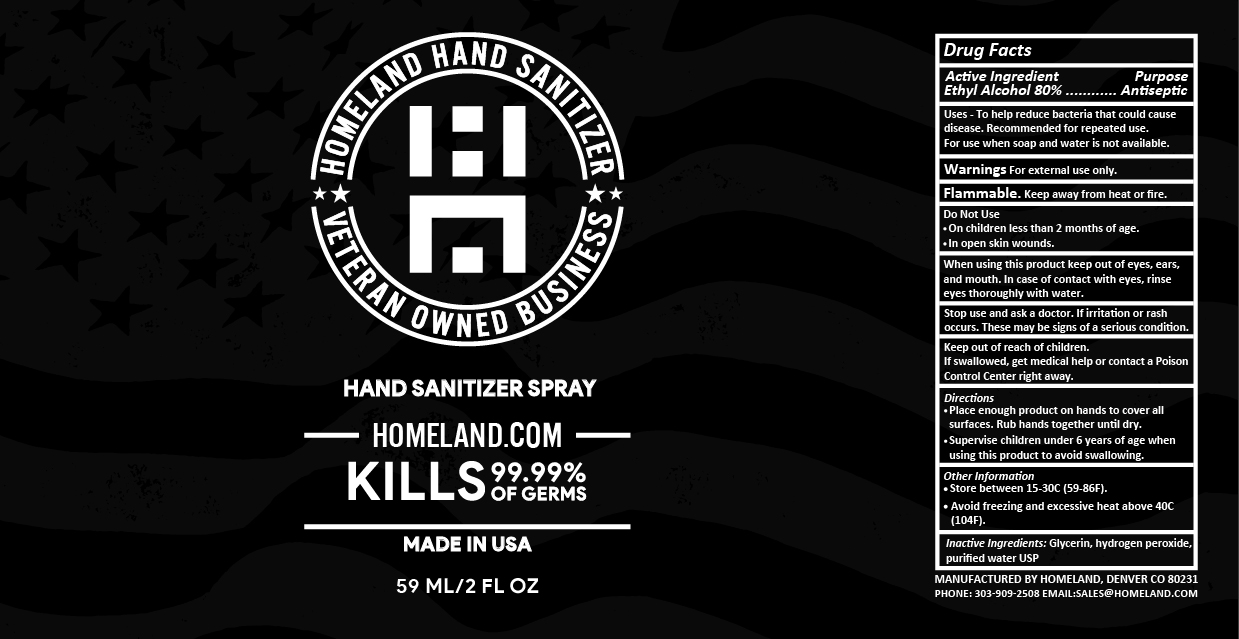 DRUG LABEL: Homeland Hand Sanitizer
NDC: 78838-004 | Form: SPRAY
Manufacturer: Pillow Menu LLC
Category: otc | Type: HUMAN OTC DRUG LABEL
Date: 20201111

ACTIVE INGREDIENTS: ALCOHOL 0.8 mL/1 mL
INACTIVE INGREDIENTS: GLYCERIN; HYDROGEN PEROXIDE; WATER

Homeland Hand Sanitizer Spray

Active Ingredient

Ethyl Alcohol 80%

Purpose

Antiseptic

Uses

- To help reduce bacteria that could cause disease. Recommended for repeated use. For use when soap and water is not available.

Warnings

For external use only.

Flammable. Keep away from heat or fire.

Do Not Use

- On children less than 2 months of age.
- In open skin wounds.

When using this product

keep out of eyes, ears, and mouth. In case of contact with eyes, rinse eyes thoroughly with water.

Stop use and ask a doctor.

If irritation or rash occurs. These may be signs of a serious condition.

Keep out of reach of children.

If swallowed, get medical help or contact a Poison Control Center right away.

Directions

- Place enough product on hands to cover all surfaces. Rub hands together until dry.
- Supervise children under 6 years of age when using this product to avoid swallowing.

Other Information

- Store between 15-30C (59-86F).
- Avoid freezing and excessive heat above 40C (104F).

Inactive Ingredients:

Glycerin, hydrogen peroxide, purified water USP